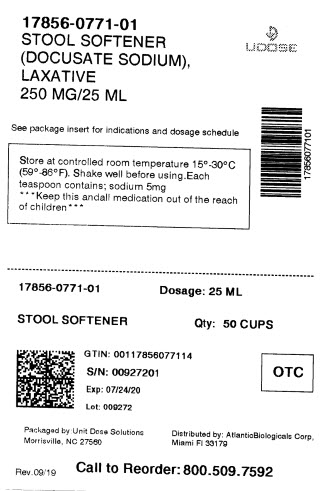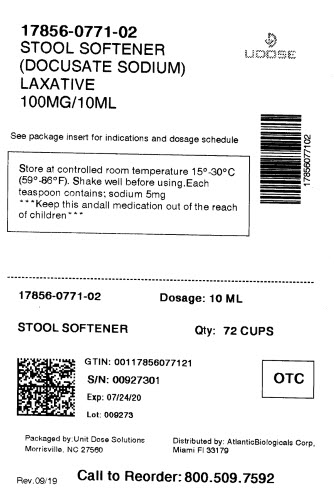 DRUG LABEL: Docu Liquid
NDC: 17856-0771 | Form: LIQUID
Manufacturer: ATLANTIC BIOLOGICALS CORP.
Category: otc | Type: HUMAN OTC DRUG LABEL
Date: 20250731

ACTIVE INGREDIENTS: DOCUSATE SODIUM 50 mg/5 mL
INACTIVE INGREDIENTS: D&C RED NO. 33; METHYLPARABEN; POLYETHYLENE GLYCOL 400; PROPYLENE GLYCOL; PROPYLPARABEN; SODIUM BENZOATE; SODIUM CITRATE, UNSPECIFIED FORM; WATER; POLOXAMER 181

Drug Facts

Active ingredient

Docusate Sodium 50 mg

Purpose

Stool Softener Laxative

Uses

- relieves occasional constipation
- generally produces bowel movement in 12-72

Warnings

Do Not Use

- if you are presently taking mineral oil
- when abdominal pain, nausea, or vomiting are present
- for longer than one week

Ask a doctor before use if you have

noticed a sudden change in bowel habits that lasts over two weeks.

Ask a doctor or pharmacist before use if you are

taking any other drug. Take this product two or more hours before or after other drugs. Laxatives may affect how other drugs work.

Stop use and ask a doctor if

- you have rectal bleeding
- you fail to have a bowel movement after use of this product

These may indicate a serious condition.

If pregnant or breast-feeding,

ask a health professional before use.

Keep Out of Reach of Children

In case of overdose, get medical help or contact a Poison Control Center right away.

Directions

- may be taken once daily or in divided doses
- give dose in 1/2 glass of milk, fruit juice or infant formula to mask bitter taste and prevent throat irritation

adults and children over 12 | 1 to 7 teaspoons
children 2 to under 12 | 1 to 3 teaspoons
children under 2 | ask a doctor

Other information

- each teaspoon contains:sodium 5 mg
- shake well before using
- store at controlled room temperature 15° - 30°C (59° - 86°F)
- dispense contents with a child resistant closure in a tight, light resistant container as defined in the USP
- store in an upright position

Inactive Ingredients

D&C Red #33, methylparaben, natural & artificial vanilla flavor, poloxamer 181, polyethylene glycol, propylene glycol, propylparaben, purified water, sodium benzoate. Sodium citrate may be used to adjust pH.

Questions or comments?

DISTRIBUTED BY:

ATLANTIC BIOLOGICALS CORP.

20101 N.E 16TH PLACE

MIAMI, FL 33179